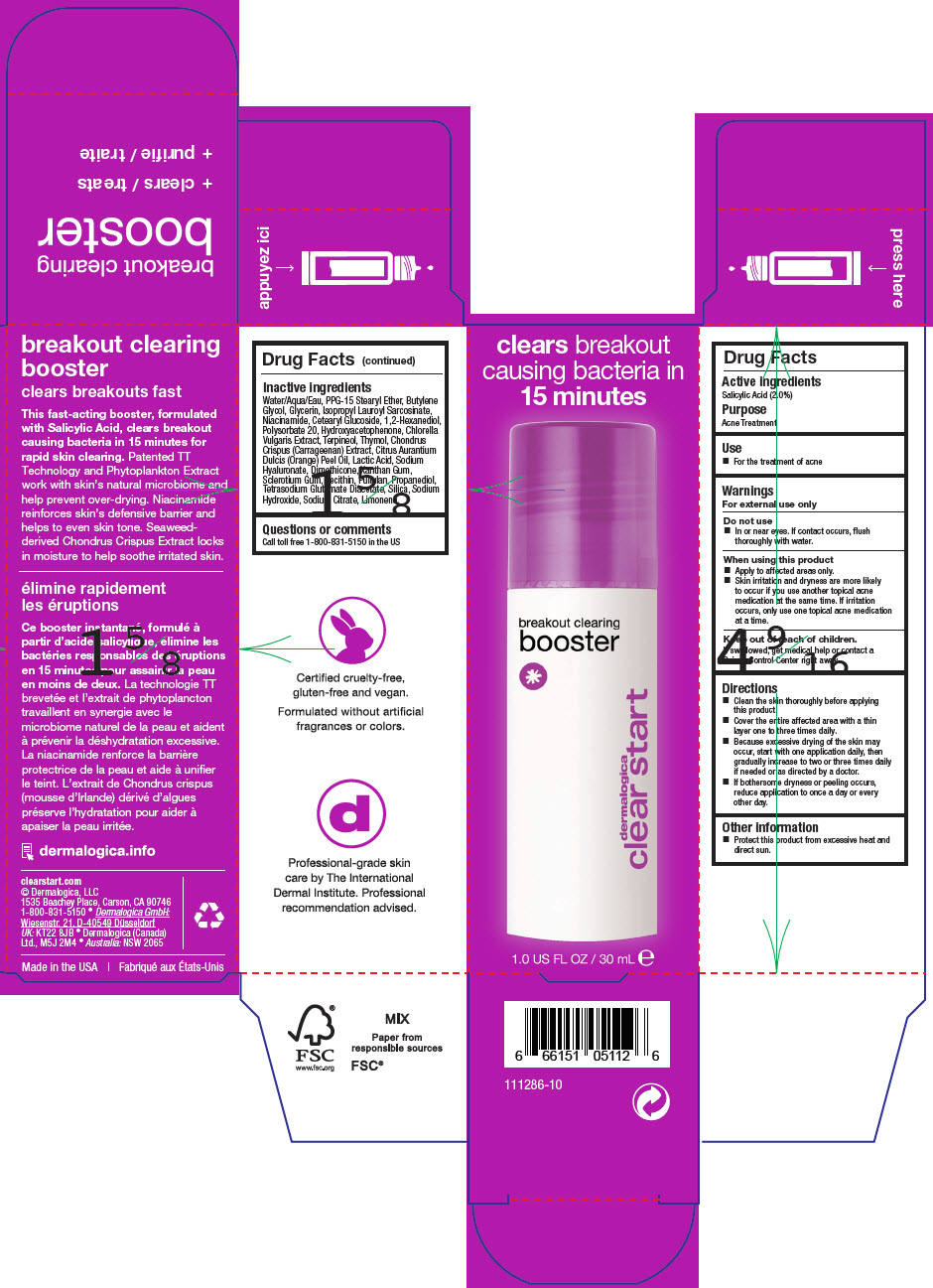 DRUG LABEL: BREAKOUT CLEARING BOOSTER
NDC: 68479-772 | Form: LIQUID
Manufacturer: Dermalogica, Inc.
Category: otc | Type: HUMAN OTC DRUG LABEL
Date: 20241224

ACTIVE INGREDIENTS: Salicylic Acid 2 mg/100 mL
INACTIVE INGREDIENTS: Water; POLYPROPYLENE GLYCOL 15 STEARYL ETHER; Butylene Glycol; Glycerin; Isopropyl Lauroyl Sarcosinate; Niacinamide; Cetearyl Glucoside; 1,2-Hexanediol; Polysorbate 20; Hydroxyacetophenone; Dimethicone; Xanthan Gum; BETASIZOFIRAN; SOYBEAN LECITHIN; Propanediol; SODIUM CITRATE, UNSPECIFIED FORM; Pullulan; CHONDRUS CRISPUS; CITRUS SINENSIS FLOWER OIL; Terpineol; Thymol; Tetrasodium Glutamate Diacetate; SILICON DIOXIDE; CHLORELLA VULGARIS; LACTIC ACID, DL-; HYALURONATE SODIUM; Sodium Hydroxide; LIMONENE, (+)-

BREAKOUT CLEARING BOOSTER

Drug Facts

Active ingredients

Salicylic Acid (2.0%)

Purpose

Acne Treatment

Use

- For the treatment of acne

Warnings

For external use only

Do not use

- In or near eyes. If contact occurs, flush thoroughly with water.

When using this product

- Apply to affected areas only.
- Skin irritation and dryness are more likely to occur if you use another topical acne medication at the same time. If irritation occurs, only use one topical acne medication at a time.

Keep out of reach of children.

If swallowed, get medical help or contact a Poison Control Center right away.

Directions

- Clean the skin thoroughly before applying this product.
- Cover the entire affected area with a thin layer one to three times daily.
- Because excessive drying of the skin may occur, start with one application daily, then gradually increase to two or three times daily if needed or as directed by a doctor.
- If bothersome dryness or peeling occurs, reduce application to once a day or every other day.

Other information

- Protect this product from excessive heat and direct sun.

Inactive ingredients

Water/Aqua/Eau, PPG-15 Stearyl Ether, Butylene Glycol, Glycerin, Isopropyl Lauroyl Sarcosinate, Niacinamide, Cetearyl Glucoside, 1,2-Hexanediol, Polysorbate 20, Hydroxyacetophenone, Chlorella Vulgaris Extract, Terpineol, Thymol, Chondrus Crispus (Carrageenan) Extract, Citrus Aurantium Dulcis (Orange) Peel Oil, Lactic Acid, Sodium Hyaluronate, Dimethicone, Xanthan Gum, Sclerotium Gum, Lecithin, Pullulan, Propanediol, Tetrasodium Glutamate Diacetate, Silica, Sodium Hydroxide, Sodium Citrate, Limonene.

Questions or comments

Call toll free 1-800-831-5150 in the US

PRINCIPAL DISPLAY PANEL - 30 mL Bottle Carton

clears breakout
causing bacteria in
15 minutes

breakout clearing
booster

dermatologica
clear start

1.0 US FL OZ / 30 mL e